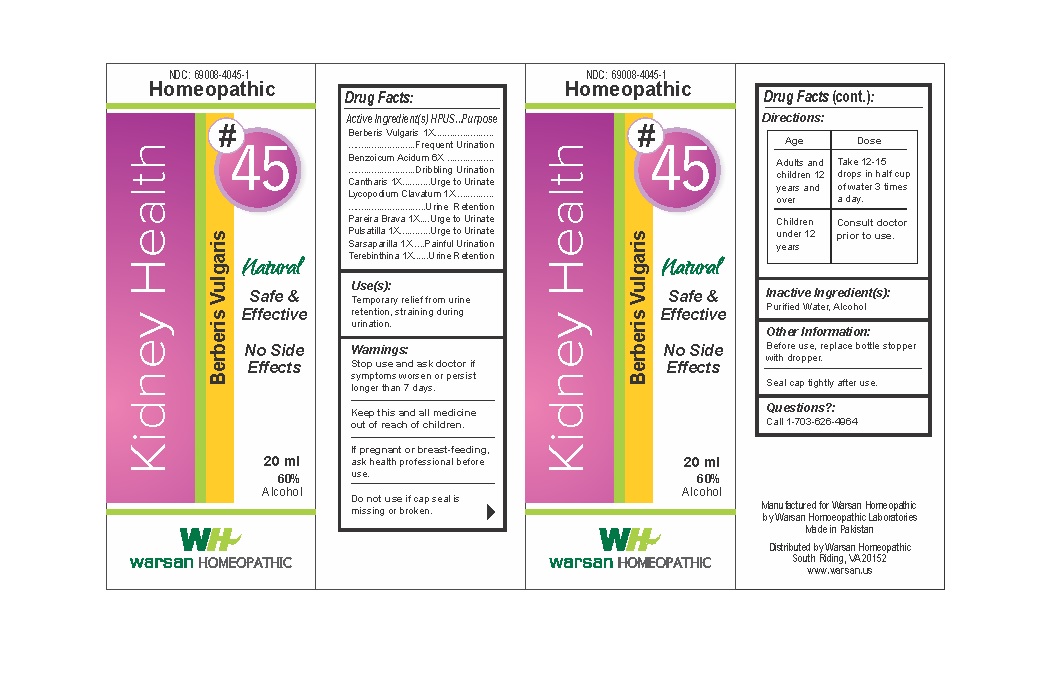 DRUG LABEL: Combination Remedy 45 - Kidney Health
NDC: 69008-4045 | Form: SOLUTION/ DROPS
Manufacturer: Warsan Homoeopathic Laboratories
Category: homeopathic | Type: HUMAN OTC DRUG LABEL
Date: 20171225

ACTIVE INGREDIENTS: LYTTA VESICATORIA 1 [hp_X]/1 mL; LYCOPODIUM CLAVATUM SPORE 1 [hp_X]/1 mL; BERBERIS VULGARIS ROOT BARK 1 [hp_X]/1 mL; PULSATILLA VULGARIS 1 [hp_X]/1 mL; SARSAPARILLA 1 [hp_X]/1 mL; BENZOIC ACID 6 [hp_X]/1 mL; CHONDRODENDRON TOMENTOSUM ROOT 1 [hp_X]/1 mL; TURPENTINE OIL 1 [hp_X]/1 mL
INACTIVE INGREDIENTS: ALCOHOL; WATER

Stop use and ask doctor if symptoms worsen or persist longer than 7 days.

If pregnant or breast-feeding, ask health professional before use.

Do not use if tamper evident seal is missing or broken.

Keep out of reach of children.

ACTIVE INGREDIENT

Berberis Vulgaris 1X

Benzoicum Acidum 6X

Cantharis 1X

Lycopodium Clavatum 1X

Pareira Brava 1X

Pulsatilla 1X

Sarsaparilla 1X

Terebinthina 1X

PURPOSE

Temporary relief from urine retention, straining during urination.

INACTIVE INGREDIENT

Purified Water

Alcohol

DOSAGE AND ADMINISTRATION

Adults and children 12 years and older: Take 10-15 drops in half cup of water 3 times a day.

Children 2 years to under 12 years: Take 8-10 drops in half cup of water of 3 times a day.

Children under 2 years: Consult doctor prior to use.

INDICATIONS AND USAGE

Temporary relief from urine retention, straining during urination.